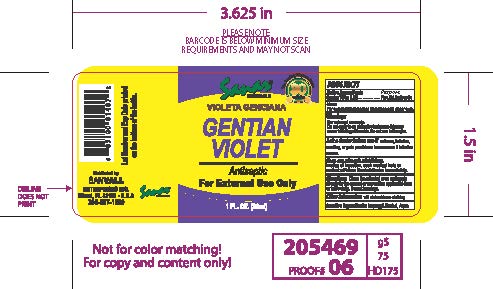 DRUG LABEL: Sanar Naturals Gentian Violet
NDC: 73386-152 | Form: TINCTURE
Manufacturer: Sanvall Enterprises, Inc
Category: otc | Type: HUMAN OTC DRUG LABEL
Date: 20241031

ACTIVE INGREDIENTS: GENTIAN VIOLET 0.1 mg/100 mL
INACTIVE INGREDIENTS: ISOPROPYL ALCOHOL; WATER

Sanar Naturals Gentian Violet

Active ingredient

Gentian Violet 0.1%

Purpose

First Aid Antiseptic

Uses

For external treatment of abrasions and minor cuts.

Warnings

For external treatment of abrasions and minor cuts

Do not

Do not apply to an ulcerative lesions as this may cause tattooing of the skin. Do not use in eyes

Stop use and ask a doctor if

redness, irritation, swelling, or pain persists or increases or if infection occurs.

Keep out of reach of children.

In case of ingestion, seek medical help or contact Poison Control Center immediately.

Directions

- Clean the affected area and apply directly to the wound or use a cotton applicator once or twice daily. Do not bandage.

Other Information

Will stain skin or clothing

Inactive ingredients

Isopropyl Alcohol, Aqua